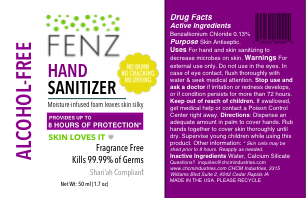 DRUG LABEL: Fenz Hand Sanitizer
NDC: 71315-120 | Form: LIQUID
Manufacturer: CHCM Industries
Category: otc | Type: HUMAN OTC DRUG LABEL
Date: 20180829

ACTIVE INGREDIENTS: BENZALKONIUM CHLORIDE 0.13 g/100 mL
INACTIVE INGREDIENTS: WATER 99.83 g/100 mL; CALCIUM SILICATE 0.04 g/100 mL

FENZ Hand Sanitizer

Active Ingredients

Benzalkonium Chloride..... 0.13%

Purpose

Skin Antiseptic

Uses

For hand and skin sanitizing to decrease microbes on skin.

Warnings

For external use only. Do not use in the eyes. In case of eye contact, flush thoroughly with water & seek medical attention.

Stop use and ask a doctor if irritation or redness develops, or if condition persists for more than 72 hours.

Keep out of reach of children

If swallowed, get medical help or contact a Poison Control Center right away.

Directions

Dispense an adequate amount in palm to cover hands. Rub hands together to cover skin thoroughly until dry. Supervise young children while using this product.

Other Information

Skin cells may be shed naturally or by abrasion prior to 8 hours, exposing fresh, unprotected skin. Reapply as needed.

Inactive Ingredients

Water, Calcium Silicate

Questions?

inquiries@chcmindustries.com

www.chcmindustries.com

CHCM Industries

3315 Williams Blvd Suite 2, #242

Cedar Rapids, IA

Moisture-infused foam leaves skin silky

- No Burn
- No Cracking
- No Drying
- Alcohol Free
- Provides up to 8 hours of protection*
- Skin Loves It
- Fragrance Free
- Leaves Skin Soft
- Won't Dry Skin
- Kills 99.99% of germs
- Shari'ah Compliant
- Net Wt 50 mL